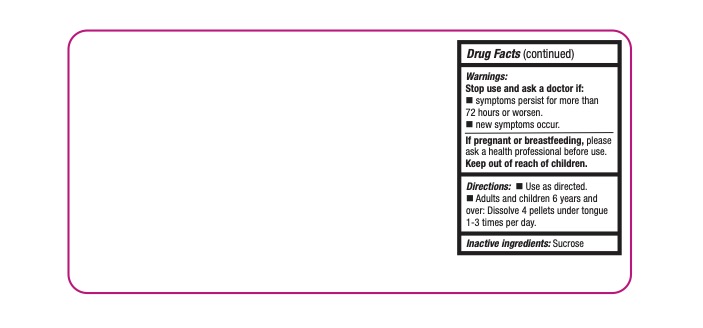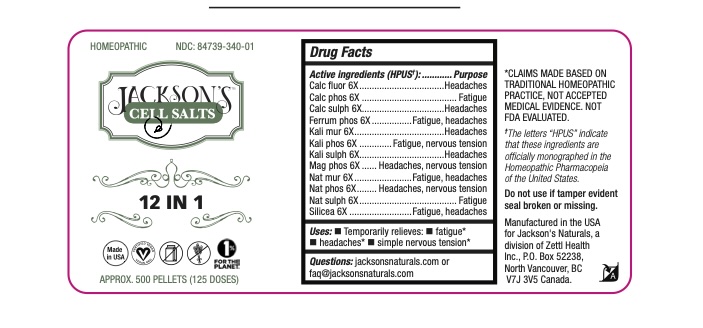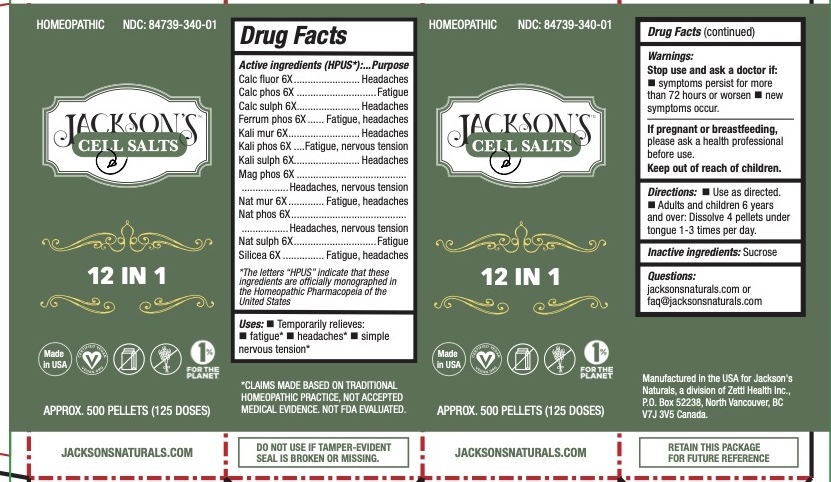 DRUG LABEL: Jacksons Cell Salts 	
NDC: 84739-340 | Form: PELLET
Manufacturer: Zettl Health Inc.
Category: homeopathic | Type: HUMAN OTC DRUG LABEL
Date: 20250204

ACTIVE INGREDIENTS: FERROSOFERRIC PHOSPHATE 6 [hp_X]/6 [hp_X]; SODIUM SULFATE 6 [hp_X]/6 [hp_X]; CALCIUM SULFATE ANHYDROUS 6 [hp_X]/6 [hp_X]; CALCIUM FLUORIDE 6 [hp_X]/6 [hp_X]; SILICON DIOXIDE 6 [hp_X]/6 [hp_X]; POTASSIUM CHLORIDE 6 [hp_X]/6 [hp_X]; SODIUM CHLORIDE 6 [hp_X]/6 [hp_X]; MAGNESIUM PHOSPHATE, DIBASIC TRIHYDRATE 6 [hp_X]/6 [hp_X]; SODIUM PHOSPHATE, DIBASIC, HEPTAHYDRATE 6 [hp_X]/6 [hp_X]; POTASSIUM PHOSPHATE 6 [hp_X]/6 [hp_X]; POTASSIUM SULFATE 6 [hp_X]/6 [hp_X]; TRIBASIC CALCIUM PHOSPHATE 6 [hp_X]/6 [hp_X]
INACTIVE INGREDIENTS: SUCROSE

Jackson's Cell Salts

Active Ingredients

Calc fluor 6X, Calc phos 6X, Calc sulph 6X, Ferrum phos , Kali mur 6X, Kali phos 6X, Kali sulph 6X, Mag phos 6X, Nat mur 6X, Nat phos 6X, Nat sulph 6X, Silicea 6X

Purpose

Calc fluor - Headaches

Calc phos - Fatigue

Calc sulph - Headaches

Ferrum phos - Fatigue, headaches

Kali mur - Headaches

Kali phos - Fatigue, nervous tension

Kali sulph - Headaches

Mag phos - Headaches, nervous tension

Nat mur - Fatigue, headaches

Nat phos - Headaches, nervous tension

Nat sulph - Fatigue

Silicea - Fatigue, headaches

Uses

Temporarily relieves:

- fatigue*
- headaches*
- simple nervous tension*

Stop use and ask a doctor if: symptoms persist for more than 72 hours or worsen

- new symptoms occur

If pregnant or breast-feeding ask a health professional before use

Keep out of reach of children

*The letters “HPUS” indicate that these ingredients are officially monographed in the Homeopathic Pharmacopeia of the United States

*CLAIMS BASED ON TRADITIONAL HOMEOPATHIC PRACTICE NOT ACCEPTED MEDICAL EVIDENCE. NOT FDA EVALUATED.

DO NOT USE IF TAMPER-EVIDENT SEAL IS BROKEN OR MISSING.

JACKSONSNATURALS.COM

Inactive Ingredients

sucrose

Directions

- Use as directed.
- Adults and children 6 years and over: Dissolve 4 pellets under tongue 1-3 times per day.

Questions:

jacksonsnaturals.com or

faq@jacksonsnaturals.com